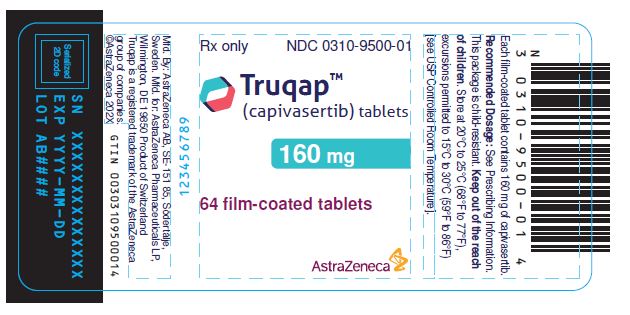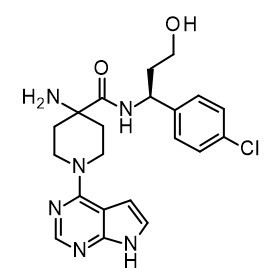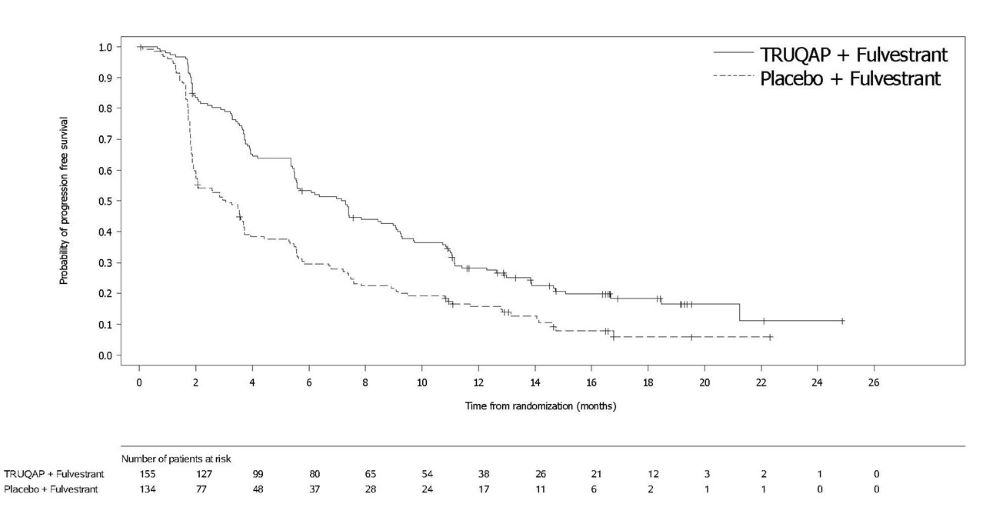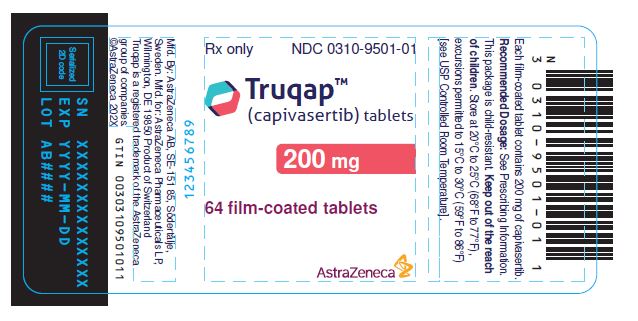 DRUG LABEL: TRUQAP
NDC: 0310-9500 | Form: TABLET, FILM COATED
Manufacturer: AstraZeneca Pharmaceuticals LP
Category: prescription | Type: HUMAN PRESCRIPTION DRUG LABEL
Date: 20251114

ACTIVE INGREDIENTS: CAPIVASERTIB 160 mg/1 1
INACTIVE INGREDIENTS: MICROCRYSTALLINE CELLULOSE; ANHYDROUS DIBASIC CALCIUM PHOSPHATE; CROSCARMELLOSE SODIUM; MAGNESIUM STEARATE; HYPROMELLOSE, UNSPECIFIED; COPOVIDONE K25-31; POLYETHYLENE GLYCOL 3350; POLYDEXTROSE; MEDIUM-CHAIN TRIGLYCERIDES; TITANIUM DIOXIDE; FERRIC OXIDE YELLOW; FERRIC OXIDE RED; FERROSOFERRIC OXIDE; WATER

HIGHLIGHTS OF PRESCRIBING INFORMATION

These highlights do not include all the information needed to use TRUQAP safely and effectively. See full prescribing information for TRUQAP.
TRUQAP® (capivasertib) tablets, for oral use
Initial U.S. Approval: 2023

RECENT MAJOR CHANGES

Warnings and Precautions, Hyperglycemia (5.1) 02/2025

1 INDICATIONS AND USAGE

TRUQAP is a kinase inhibitor indicated, in combination with fulvestrant for the treatment of adult patients with hormone receptor (HR)-positive, human epidermal growth factor receptor 2 (HER2)-negative, locally advanced or metastatic breast cancer with one or more PIK3CA/AKT1/PTEN-alterations as detected by an FDA-approved test following progression on at least one endocrine-based regimen in the metastatic setting or recurrence on or within 12 months of completing adjuvant therapy. (1)

2 DOSAGE AND ADMINISTRATION

- Select patients for the treatment of HR-positive, HER2-negative advanced or metastatic breast cancer with TRUQAP based on the presence of one or more of the following genetic alterations in tumor tissue: PIK3CA/AKT1/PTEN. (2.1)
- Recommended Dosage: 400 mg orally twice daily, with or without food, for 4 days followed by 3 days off. (2.3)

3 DOSAGE FORMS AND STRENGTHS

Tablets: 160 mg and 200 mg (3)

4 CONTRAINDICATIONS

Severe hypersensitivity to TRUQAP or any of its components. (4)

5 WARNINGS AND PRECAUTIONS

- Hyperglycemia: TRUQAP can cause hyperglycemia. Evaluate blood glucose levels prior to starting and at regular intervals during treatment. Withhold, reduce dose, or permanently discontinue TRUQAP based on severity. (2.2, 2.4, 5.1)
- Diarrhea: TRUQAP caused diarrhea in most patients. Advise patients to increase oral fluids, start antidiarrheal treatment, and consult with a healthcare provider if diarrhea occurs while taking TRUQAP. Withhold, reduce dose, or permanently discontinue TRUQAP based on severity. (2.4, 5.2)
- Cutaneous Adverse Reactions: Monitor for signs and symptoms of cutaneous adverse reactions. Withhold, reduce dose, or permanently discontinue TRUQAP based on severity. (2.4, 5.3)
- Embryo-Fetal Toxicity: TRUQAP can cause fetal harm. Advise patients of potential risk to a fetus and to use effective contraception. Refer to the Full Prescribing Information of fulvestrant for pregnancy and contraception information. (5.4, 8.1, 8.3)

6 ADVERSE REACTIONS

Most common adverse reactions (incidence ≥20%), including laboratory abnormalities, were diarrhea, cutaneous adverse reactions, increased random glucose, decreased lymphocytes, decreased hemoglobin, increased fasting glucose, nausea, fatigue, decreased leukocytes, increased triglycerides, decreased neutrophils, increased creatinine, vomiting and stomatitis. (6.1)

To report SUSPECTED ADVERSE REACTIONS, contact AstraZeneca at 1-800-236-9933 or FDA at 1-800-FDA-1088 or www.fda.gov/medwatch.

7 DRUG INTERACTIONS

- Strong CYP3A Inhibitors: Avoid concomitant use. If concomitant use cannot be avoided, reduce TRUQAP dose. (2.5, 7.1)
- Moderate CYP3A Inhibitors: Reduce TRUQAP dose. (2.5, 7.1)
- Strong and Moderate CYP3A Inducers: Avoid concomitant use. (7.1)

8 USE IN SPECIFIC POPULATIONS

Lactation: Advise not to breastfeed. (8.2)

FULL PRESCRIBING INFORMATION

1 INDICATIONS AND USAGE

TRUQAP, in combination with fulvestrant, is indicated for the treatment of adult patients with hormone receptor (HR)-positive, human epidermal growth factor receptor 2 (HER2)-negative, locally advanced or metastatic breast cancer with one or more PIK3CA/AKT1/PTEN-alteration as detected by an FDA-approved test following progression on at least one endocrine-based regimen in the metastatic setting or recurrence on or within 12 months of completing adjuvant therapy.

2 DOSAGE AND ADMINISTRATION

2.1 Patient Selection

Select patients for the treatment of HR-positive, HER2-negative advanced or metastatic breast cancer with TRUQAP, based on the presence of one or more of the following genetic alterations in tumor tissue: PIK3CA/AKT1/PTEN [see Clinical Studies (14)].

Information on FDA-approved tests for the detection of PIK3CA, AKT1, and PTEN alterations is available at: http://www.fda.gov/CompanionDiagnostics.

2.2 Recommended Evaluation Before Initiating TRUQAP

Evaluate fasting blood glucose (FG) and hemoglobin A1C (HbA1C) prior to starting TRUQAP and at regular intervals during treatment [see Warnings and Precautions (5.1)].

2.3 Recommended Dosage and Administration

The recommended dosage of TRUQAP, in combination with fulvestrant, is 400 mg orally twice daily (approximately 12 hours apart) with or without food, for 4 days followed by 3 days off. Continue TRUQAP until disease progression or unacceptable toxicity.

TRUQAP dosing schedule for each week is provided in Table 1.

Table 1: TRUQAP Dosing Schedule for Each Week
Day | 1 | 2 | 3 | 4 | 5 [No dosing on day 5, 6 and 7.] | 6 | 7
Morning | 2 x 200 mg | 2 x 200 mg | 2 x 200 mg | 2 x 200 mg
Evening | 2 x 200 mg | 2 x 200 mg | 2 x 200 mg | 2 x 200 mg

Swallow TRUQAP tablets whole. Do not chew, crush, or split tablets prior to swallowing. Do not take tablets that are broken, cracked, or otherwise not intact.

If a patient misses a dose within 4 hours of the scheduled time, instruct the patient to take the missed dose. If a patient misses a dose more than 4 hours of the scheduled time, instruct the patient to skip the dose and take the next dose at its usual scheduled time.

If a patient vomits a dose, instruct the patient not to take an additional dose and take the next dose at its usual scheduled time.

Refer to the fulvestrant Full Prescribing Information for recommended fulvestrant dosing information.

For premenopausal and perimenopausal women, administer a luteinizing hormone-releasing hormone (LHRH) agonist according to current clinical practice standards.

For men, consider administering a LHRH agonist according to current clinical practice standards.

2.4 Dosage Modifications for Adverse Reactions

The recommended dose reductions for adverse reactions are listed in Table 2. Permanently discontinue TRUQAP if unable to tolerate the second dose reduction.

Table 2: Recommended Dose Reductions of TRUQAP for Adverse Reactions
TRUQAP | Dose and Schedule
First dose reduction | 320 mg twice daily for 4 days followed by 3 days off
Second dose reduction | 200 mg twice daily for 4 days followed by 3 days off

The recommended dosage modifications for adverse reactions are provided in Table 3.

Table 3: Recommended Dosage Modifications of TRUQAP for Adverse Reactions
Adverse Reaction | Severity [Severity grading according to Common Terminology Criteria for Adverse Events (CTCAE) Version 5.0.] | TRUQAP Dosage Modification
Hyperglycemia [For the management of suspected or confirmed diabetic ketoacidosis (DKA) refer to section Warnings and Precautions (5.1).]; (Fasting Glucose [FG]); [see Warnings and Precautions (5.1)] | FG > ULN‑160 mg/dL; or; FG > ULN‑8.9 mmol/L; or; HbA1C > 7% | Consider initiation or intensification of oral anti-diabetic treatment.
Hyperglycemia [For the management of suspected or confirmed diabetic ketoacidosis (DKA) refer to section Warnings and Precautions (5.1).]; (Fasting Glucose [FG]); [see Warnings and Precautions (5.1)] | FG 161‑250 mg/dL; or; FG 9‑13.9 mmol/L | Withhold TRUQAP until FG decrease ≤ 160 mg/dL (or ≤ 8.9 mmol/L).; If recovery occurs in ≤ 28 days, resume TRUQAP at same dose.; If recovery occurs in > 28 days, resume TRUQAP at one lower dose.
Hyperglycemia [For the management of suspected or confirmed diabetic ketoacidosis (DKA) refer to section Warnings and Precautions (5.1).]; (Fasting Glucose [FG]); [see Warnings and Precautions (5.1)] | FG 251‑500 mg/dL; or; FG 14‑27.8 mmol/L | Withhold TRUQAP until FG decrease ≤ 160 mg/dL (or ≤ 8.9 mmol/L).; If recovery occurs in ≤ 28 days, resume TRUQAP at one lower dose.; If recovery occurs in > 28 days, permanently discontinue TRUQAP.
Hyperglycemia [For the management of suspected or confirmed diabetic ketoacidosis (DKA) refer to section Warnings and Precautions (5.1).]; (Fasting Glucose [FG]); [see Warnings and Precautions (5.1)] | FG > 500 mg/dL; or; FG > 27.8 mmol/L; or; life-threatening sequelae of hyperglycemia at any FG level | Withhold TRUQAP.; For life-threatening sequelae of hyperglycemia or if FG persists at ≥ 500 mg/dL after 24 hours, permanently discontinue TRUQAP.; If FG ≤ 500 mg/dL (or ≤ 27.8 mmol/L) within 24 hours, then follow the guidance in the table for the relevant grade
Diarrhea; [see Warnings and Precautions (5.2)] | Grade 2 | Withhold TRUQAP until recovery to ≤ Grade 1.; If recovery occurs in ≤ 28 days, resume TRUQAP at same dose or one lower dose as clinically indicated.; If recovery occurs in > 28 days, resume at one lower dose as clinically indicated.; For recurrence, reduce TRUQAP by one lower dose.
Diarrhea; [see Warnings and Precautions (5.2)] | Grade 3 | Withhold TRUQAP until recovery to ≤ Grade 1. If recovery occurs in ≤ 28 days, resume TRUQAP at same dose or one lower dose as clinically indicated.; If recovery occurs in > 28 days, permanently discontinue TRUQAP.
Diarrhea; [see Warnings and Precautions (5.2)] | Grade 4 | Permanently discontinue TRUQAP.
Cutaneous Adverse Reactions; [see Warnings and Precautions (5.3)] | Grade 2 | Withhold TRUQAP until recovery to ≤ Grade 1.; Resume TRUQAP at the same dose.; Persistent or recurrent: reduce TRUQAP by one lower dose.
Cutaneous Adverse Reactions; [see Warnings and Precautions (5.3)] | Grade 3 | Withhold TRUQAP until recovery to ≤ Grade 1.; If recovery occurs in ≤ 28 days, resume TRUQAP at same dose.; If recovery occurs in > 28 days, resume TRUQAP at one lower dose.; For recurrent Grade 3, permanently discontinue TRUQAP.
Cutaneous Adverse Reactions; [see Warnings and Precautions (5.3)] | Grade 4 | Permanently discontinue TRUQAP.
Other Adverse Reactions; [see Adverse Reactions (6.1)] | Grade 2 | Withhold TRUQAP until recovery to ≤ Grade 1.; Resume TRUQAP at the same dose.
Other Adverse Reactions; [see Adverse Reactions (6.1)] | Grade 3 | Withhold TRUQAP until recovery to ≤ Grade 1. If recovery occurs in ≤ 28 days, resume TRUQAP at same dose.; If recovery occurs in > 28 days, resume TRUQAP at one lower dose.
Other Adverse Reactions; [see Adverse Reactions (6.1)] | Grade 4 | Permanently discontinue TRUQAP.

2.5 Dosage Modifications for Strong and Moderate CYP3A Inhibitors

Avoid concomitant use with strong CYP3A inhibitors. If concomitant use with a strong CYP3A inhibitor cannot be avoided, reduce the dosage of TRUQAP to 320 mg orally twice daily for 4 days followed by 3 days off [see Drug Interactions (7.1)].

When concomitantly used with a moderate CYP3A inhibitor, reduce the dosage of TRUQAP to 320 mg orally twice daily for 4 days followed by 3 days off.

After discontinuation of a strong or moderate CYP3A inhibitor, resume the TRUQAP dosage (after 3 to 5 half-lives of the inhibitor) that was taken prior to initiating the strong or moderate CYP3A inhibitor.

3 DOSAGE FORMS AND STRENGTHS

Tablets:

- 160 mg: beige film-coated, round, biconvex tablets debossed with ‘CAV’ above ‘160’ on one side and plain on the reverse.
- 200 mg: beige film-coated, capsule-shaped, biconvex tablets debossed with ‘CAV 200’ on one side and plain on the reverse.

4 CONTRAINDICATIONS

TRUQAP is contraindicated in patients with severe hypersensitivity to TRUQAP or any of its components.

5 WARNINGS AND PRECAUTIONS

5.1 Hyperglycemia

Severe hyperglycemia, including diabetic ketoacidosis and fatal outcomes, can occur in patients treated with TRUQAP.

Increased fasting glucose from baseline occurred in 37% of patients treated with TRUQAP, including 11% of patients with Grade 2 (FG > 160 to 250 mg/dL), 2% with Grade 3 (FG > 250 to 500 mg/dL), and 1.1% with Grade 4 (FG > 500 mg/dL) events.

The median time to first occurrence of hyperglycemia was 15 days (range: 1 to 367). Dose reduction for hyperglycemia was required in 0.6% of patients and permanent discontinuation was required in 0.6% of patients.

Diabetic ketoacidosis occurred in 0.3% of patients and diabetic metabolic decompensation in 0.6% of patients.

In CAPItello-291, 12% (43/355) of patients who received TRUQAP had an anti-hyperglycemic medication regimen either initiated or changed during the study, including treatment with insulin in 4.8% (17/355) of patients.

The safety of TRUQAP has not been established in patients with Type I diabetes or diabetes requiring insulin. Patients with insulin-dependent diabetes were excluded from CAPItello-291.

Before initiating treatment with TRUQAP, test fasting glucose levels (FPG or FBG), HbA1C levels, and optimize fasting glucose.

After initiating treatment with TRUQAP, monitor or self-monitor fasting glucose levels on Day 3 or 4 of the dosing week during weeks 1, 2, 4, 6 and 8; then monthly while on treatment with TRUQAP; and as clinically indicated. Monitor HbA1C levels every 3 months during treatment with TRUQAP and as clinically indicated. Patients with a history of well-controlled Type 2 diabetes mellitus may require intensified anti-hyperglycemic treatment and close monitoring of fasting glucose levels.

For patients who experience hyperglycemia during treatment with TRUQAP, monitor fasting glucose at least twice weekly, on days on and off TRUQAP, until fasting glucose decreases to baseline levels. During treatment with anti-diabetic medications, monitor fasting glucose at least once a week for 2 months, followed by once every 2 weeks, or as clinically indicated.

Consider consultation with a healthcare practitioner with expertise in the treatment of hyperglycemia and initiation of fasting glucose monitoring at home for patients who have risk factors for hyperglycemia or who experience hyperglycemia. Advise patients of the signs and symptoms of hyperglycemia and counsel patients on lifestyle changes.

Withhold TRUQAP immediately when ketoacidosis is suspected. If ketoacidosis is confirmed, permanently discontinue TRUQAP.

Based on the severity of the hyperglycemia, withhold, reduce dose, or permanently discontinue TRUQAP [see Dosage and Administration (2.4)].

5.2 Diarrhea

Severe diarrhea associated with dehydration occurred in patients who received TRUQAP.

Diarrhea occurred in 72% of patients. Grade 3 or 4 diarrhea occurred in 9% of patients. The median time to first occurrence was 8 days (range 1 to 519). In the 257 patients with diarrhea, 59% required anti-diarrheal medications to manage symptoms. Dose reductions were required in 8% of patients, and 2% of patients permanently discontinued TRUQAP due to diarrhea. In patients with Grade ≥ 2 diarrhea (n=93) with at least 1 grade improvement (n=89), median time to improvement from the first event was 4 days (range: 1 to 154).

Monitor patients for signs and symptoms of diarrhea. Advise patients to increase oral fluids and start antidiarrheal treatment at the first sign of diarrhea while taking TRUQAP. Withhold, reduce dose, or permanently discontinue TRUQAP based on severity [see Dosage and Administration (2.4)].

5.3 Cutaneous Adverse Reactions

Cutaneous adverse reactions, which can be severe, including erythema multiforme (EM), palmar-plantar erythrodysesthesia, and drug reaction with eosinophilia and systemic symptoms (DRESS), occurred in patients who received TRUQAP.

Cutaneous adverse reactions occurred in 58% of patients. Grade 3 or 4 cutaneous adverse reactions occurred in 17% of patients receiving TRUQAP. EM occurred in 1.7% of patients and DRESS occurred in 0.3% of patients. Dose reduction was required in 7% of patients and 7% of patients permanently discontinued TRUQAP due to cutaneous adverse reactions.

The median time to onset of cutaneous adverse reactions was 13 days (range 1 to 575 days). Among the 204 patients with cutaneous adverse reactions, 44% (90/204) required corticosteroid treatment. Of these, 37% (76/204) were treated with topical corticosteroids and 19% (39/204) with systemic corticosteroids. In patients with Grade ≥ 2 cutaneous adverse reaction (n= 116) with at least 1 grade improvement (n=104), median time to improvement from the first event was 12 days (range 2 to 544).

Monitor patients for signs and symptoms of cutaneous adverse reactions. Early consultation with a dermatologist is recommended. Withhold, reduce dose, or permanently discontinue TRUQAP based on severity [see Dosage and Administration (2.4)].

5.4 Embryo-Fetal Toxicity

Based on findings from animals and mechanism of action, TRUQAP can cause fetal harm when administered to a pregnant woman [see Clinical Pharmacology (12.1)]. In an animal reproduction study, oral administration of capivasertib to pregnant rats during the period of organogenesis caused adverse developmental outcomes, including embryo-fetal mortality, and reduced fetal weights at maternal exposures 0.7 times the human exposure (AUC) at the recommended dosage of 400 mg twice daily.

Advise pregnant women and females of reproductive potential of the potential risk to a fetus. Advise females of reproductive potential to use effective contraception during treatment with TRUQAP and for 1 month after the last dose. Advise male patients with female partners of reproductive potential to use effective contraception during treatment with TRUQAP and for 4 months after the last dose [see Use in Specific Populations (8.1, 8.3)].

TRUQAP is used in combination with fulvestrant. Refer to the Full Prescribing Information of fulvestrant for pregnancy and contraception information.

6 ADVERSE REACTIONS

The following adverse reactions are also discussed in greater details in other sections of the labeling:

- Hyperglycemia [see Warnings and Precautions (5.1)]
- Diarrhea [see Warnings and Precautions (5.2)]
- Cutaneous Adverse Reactions [see Warnings and Precautions (5.3)]

6.1 Clinical Trials Experience

Because clinical trials are conducted under widely varying conditions, adverse reaction rates observed in the clinical trials of a drug cannot be directly compared to rates in the clinical trials of another drug and may not reflect the rates observed in practice.

The safety population described in WARNINGS and PRECAUTIONS reflects exposure to TRUQAP 400 mg orally, twice a day for 4 days followed by 3 days off, in combination with fulvestrant, in 355 patients in CAPItello-291 until disease progression or unacceptable toxicity. Among the 355 patients who received TRUQAP, 52% were exposed for 6 months or longer, and 27% were exposed for greater than one year. In this safety population, the most common (≥ 20%) adverse reactions including laboratory abnormalities were diarrhea (72%), cutaneous adverse reactions (58%), increased random glucose (57%), decreased lymphocytes (47%), decreased hemoglobin (45%), increased fasting glucose (37%), nausea and fatigue (35% each), decreased leukocytes (32%), increased triglycerides (27%), decreased neutrophils (23%), increased creatinine (22%), vomiting (21%), and stomatitis (20%).

CAPItello-291

The safety of TRUQAP was evaluated in CAPItello-291, a clinical trial including 288 adult patients (155 patients in TRUQAP with fulvestrant arm and 133 patients in placebo with fulvestrant arm) whose breast cancer had one or more PIK3CA/AKT1/PTEN-alterations [see Clinical Studies (14)]. Among patients who received TRUQAP, 61% were exposed for 6 months or longer and 30% were exposed for greater than one year.

Of the 155 patients who received TRUQAP with fulvestrant, the median age was 58 years (range 36 to 84); female (99%); White (48%), Asian (31%), Black (1.3%), American Indian/Alaska Native (0.6%), and other races (19%).

Serious adverse reactions occurred in 18% of patients receiving TRUQAP with fulvestrant. The most common serious adverse reactions (≥ 1%) were cutaneous adverse reaction (3.9%), diarrhea and pneumonia (2.6% each), vomiting and pyrexia (1.9% each), hyperglycemia, hypersensitivity, fatigue, renal injury and second malignancy (1.3% each).

Fatal adverse reactions occurred in 1.3% of patients who received TRUQAP with fulvestrant, including sepsis (0.6%), and acute myocardial infarction (0.6%).

Permanent TRUQAP discontinuation due to an adverse reaction occurred in 10% of patients. The most common adverse reaction (≥ 2%) leading to permanent discontinuation of TRUQAP was cutaneous adverse reactions (6%). Dosage interruptions of TRUQAP due to an adverse reaction occurred in 39% of patients. Adverse reactions leading to dosage interruption in ≥ 2% of patients included cutaneous adverse reactions (14%), diarrhea (10%), pyrexia (4.5%), vomiting and nausea (3.2% each), and fatigue (2.6%).

Dose reductions of TRUQAP due to adverse reactions occurred in 21% of patients receiving TRUQAP with fulvestrant. Adverse reactions leading to TRUQAP dose reductions in ≥ 2% of patients were diarrhea and cutaneous adverse reactions (8% each).

The most common (≥ 20%) adverse reactions including laboratory abnormalities were diarrhea (77%), increased random glucose (58%), cutaneous adverse reaction (56%), decreased lymphocytes (49%), decreased hemoglobin (47%), fatigue (38%), increased fasting glucose (37%), nausea and decreased leukocytes (35% each), increased triglycerides (30%), stomatitis (25%), decreased neutrophils (25%), and vomiting (21%). Adverse reactions and laboratory abnormalities are listed in Table 4 and Table 5, respectively.

Table 4: Adverse Reactions ≥ 10% in Patients who Received TRUQAP with Fulvestrant [with a Difference Between Arms of ≥ 3%] in CAPItello-291
Adverse Reaction | TRUQAP with Fulvestrant N=155 |  | Placebo with Fulvestrant N=133
Adverse Reaction | All Grades % | Grade 3 or 4 % | All Grades % | Grade 3 or 4 %
Gastrointestinal Disorders
Diarrhea | 77 | 12 | 19 | 0.8
Nausea | 35 | 1.3 | 14 | 0.8
Stomatitis [Includes other related terms.] | 25 | 1.9 | 5 | 0
Vomiting | 21 | 1.9 | 7 | 0.8
Skin and Subcutaneous Tissue Disorders
Cutaneous adverse reactions [Cutaneous adverse reaction includes butterfly rash, dermatitis, allergic dermatitis, dry skin, eczema, erythema multiforme, hand dermatitis, palmar-plantar erythrodysesthesia syndrome, pruritus, rash, erythematous rash, maculo-papular rash, papular rash, skin discoloration, skin fissures, skin reaction, skin ulcer, urticaria, purpura, erythema and drug eruption.] | 56 | 15 | 16 | 0.8
General Disorders and Administration Site Conditions
Fatigue | 38 | 1.9 | 27 | 1.5
Metabolism and Nutrition Disorders
Decreased appetite | 17 | 0 | 8 | 0.8
Nervous System Disorders
Headache | 17 | 0 | 13 | 0.8
Infections and Infestations
Urinary tract infection | 14 | 0.6 | 5 | 0
Renal and Urinary disorders
Renal injury [Renal injury includes acute kidney injury, renal failure, renal impairment, glomerular filtration rate decreased, increased creatinine and proteinuria.] | 11 | 2.6 | 1.5 | 0.8

Clinically relevant adverse reactions occurring in < 10% of patients treated with TRUQAP included anemia, pyrexia, dysgeusia, dyspepsia, pneumonia, weight decreased, and hypersensitivity (including anaphylactic reaction).

Table 5: Laboratory Abnormalities (≥ 10%) That Worsened from Baseline in Patients who Received TRUQAP with Fulvestrant [With a Difference Between Arms ≥3%] in CAPItello-291
Laboratory Abnormality | TRUQAP with Fulvestrant [The denominator used to calculate the rate varied from 129 to 155 based on the number of patients with a baseline value and at least one post-treatment value.] |  | Placebo with Fulvestrant [The denominator used to calculate the rate varied from 109 to 131 based on the number of patients with a baseline value and at least one post-treatment value.]
Laboratory Abnormality | All Grades (%) | Grade 3 or 4 (%) | All Grades (%) | Grade 3 or 4 (%)
Glucose Metabolism
Increased random glucose | 58 | 9 | 17 | 0
Increased fasting glucose | 37 | 0.6 | 29 | 0
Hematology
Decreased lymphocytes | 49 | 11 | 14 | 2.3
Decreased hemoglobin | 47 | 2 | 22 | 2.3
Decreased leukocytes | 35 | 0.6 | 23 | 0
Decreased neutrophils | 25 | 1.9 | 16 | 0.8
Decreased platelets | 12 | 1.9 | 6 | 0.8
Other Categories
Increased triglycerides | 30 | 0.7 | 22 | 0.9
Increased alanine aminotransferase | 23 | 2.6 | 13 | 0
Electrolytes/Renal
Decreased corrected calcium | 19 | 0.6 | 8 | 0
Increased creatinine | 19 | 1.3 | 4.6 | 0.8
Decreased potassium | 17 | 4.5 | 8 | 0

7 DRUG INTERACTIONS

7.1 Effects of Other Drugs on TRUQAP

Table 6 describes drug interactions where concomitant use of another drug affects TRUQAP.

Table 6: Drug Interactions with TRUQAP
Strong CYP3A Inhibitors
Clinical Impact | - Capivasertib is a CYP3A substrate. Strong CYP3A inhibitors increase capivasertib exposure [see Clinical Pharmacology (12.3)], which may increase the risk of TRUQAP adverse reactions.
Prevention or Management | - Avoid concomitant use with a strong CYP3A inhibitor. If concomitant use cannot be avoided, reduce the dose of TRUQAP and monitor patients for adverse reactions [see Dosage and Administration (2.5)].
Moderate CYP3A Inhibitors
Clinical Impact | - Capivasertib is a CYP3A substrate. Moderate CYP3A inhibitors increase capivasertib exposure [see Clinical Pharmacology (12.3)], which may increase the risk of TRUQAP adverse reactions.
Prevention or Management | - When concomitantly used with moderate CYP3A inhibitor, reduce the dose of TRUQAP and monitor patients for adverse reactions [see Dosage and Administration (2.5)].
Strong and Moderate CYP3A Inducers
Clinical Impact | - Capivasertib is a CYP3A substrate. Strong and moderate CYP3A inducers decrease capivasertib exposure [see Clinical Pharmacology (12.3)], which may reduce the effectiveness of TRUQAP.
Prevention or Management | - Avoid concomitant use of TRUQAP with strong or moderate CYP3A inducers.

8 USE IN SPECIFIC POPULATIONS

8.1 Pregnancy

Risk Summary

TRUQAP is used in combination with fulvestrant. Refer to the Full Prescribing Information of fulvestrant for pregnancy information.

Based on findings in animals and mechanism of action, TRUQAP can cause fetal harm when administered to a pregnant woman [see Clinical Pharmacology (12.1)]. There are no available data on the use of TRUQAP in pregnant women. In an animal reproduction study, oral administration of capivasertib to pregnant rats during the period of organogenesis caused adverse developmental outcomes, including embryo-fetal mortality and reduced fetal weights at maternal exposures 0.7 times the human exposure (AUC) at the recommended dose of 400 mg twice daily (see Data). Advise pregnant women and females of reproductive potential of the potential risk to a fetus.

The background risk of major birth defects and miscarriage for the indicated population is unknown. In the U.S. general population, the estimated background risk of major birth defects is 2% to 4% and of miscarriage is 15% to 20% of clinically recognized pregnancies in the U.S. general population.

Data

Animal Data

In an embryo-fetal development study, pregnant rats received oral doses of capivasertib up to 150 mg/kg/day during the period of organogenesis. Administration of capivasertib resulted in maternal toxicities (reduced body weight gain and food consumption, increased blood glucose) and adverse developmental outcomes, including embryo-fetal deaths (post-implantation loss), reduced fetal weights, and minor fetal visceral variations at a dose of 150 mg/kg/day (0.7 times the human exposure at the recommended dose of 400 mg twice daily based on AUC).

In a pre- and post-natal assessment, pregnant rats received oral doses of capivasertib up to 150 mg/kg/day from gestation day 6 through at least lactation day 6. Administration of 150 mg/kg/day resulted in reduced litter and pup weights.

8.2 Lactation

Risk Summary

TRUQAP is used in combination with fulvestrant. Refer to the Full Prescribing Information of fulvestrant for lactation information.

There are no data on the presence of capivasertib or its metabolites in human milk or their effects on milk production or the breastfed child. Capivasertib was detected in the plasma of suckling rat pups (see Data). Because of the potential for serious adverse reactions in a breastfed child, advise women not to breastfeed during treatment with TRUQAP.

Data

Animal Data

In a pre- and post-natal assessment, when capivasertib was administered to maternal rats during the lactation period, capivasertib was detected in plasma of suckling rat pups on lactation day 7 to 8 [see Use in Specific Populations (8.1)]. Plasma concentrations in pups were up to 0.6% of concentrations in maternal plasma in the 150 mg/kg/day group.

8.3 Females and Males of Reproductive Potential

TRUQAP is used in combination with fulvestrant. Refer to the Full Prescribing Information of fulvestrant for contraception and infertility information.

TRUQAP can cause fetal harm when administered to pregnant women [see Use in Specific Populations (8.1)].

Pregnancy Testing

Verify pregnancy status of females of reproductive potential prior to initiating TRUQAP [see Use in Specific Populations (8.1)].

Contraception

Females

Advise females of reproductive potential to use effective contraception during treatment with TRUQAP and for 1 month after the last dose.

Males

Advise male patients with female partners of reproductive potential to use effective contraception during treatment with TRUQAP and for 4 months after the last dose.

8.4 Pediatric Use

The safety and effectiveness of TRUQAP have not been established in pediatric patients.

8.5 Geriatric Use

Of the 355 patients who received TRUQAP in CAPItello-291, 115 (32%) patients were ≥ 65 years of age and 24 (7%) patients were ≥ 75 years of age. No overall differences in the efficacy of TRUQAP were observed between patients ≥ 65 years of age and younger patients. Analysis of the safety of TRUQAP comparing patients ≥ 65 years of age to younger patients suggest a higher incidence of Grade 3 to 5 adverse reactions (57% versus 36%), dosage reductions (30% versus 15%), dose interruptions (57% versus 30%), and permanent discontinuations (23% versus 8%), respectively.

8.6 Renal Impairment

No dosage modification is recommended for patients with mild to moderate (creatinine clearance (CLcr) 30 to 89 mL/min) renal impairment [see Clinical Pharmacology (12.3)].

TRUQAP has not been studied in patients with severe (CLcr 15 to 29 mL/min) renal impairment.

8.7 Hepatic Impairment

No dosage modification is recommended for patients with mild hepatic impairment (bilirubin ≤ upper limit of normal (ULN) and AST > ULN or bilirubin > 1 to 1.5x ULN and any AST) [see Clinical Pharmacology (12.3)].

Monitor patients with moderate (bilirubin > 1.5 to 3x ULN and any AST) hepatic impairment for adverse reactions due to potential increased capivasertib exposure [see Warnings and Precautions (5.1, 5.2, 5.3)].

TRUQAP has not been studied in patients with severe (bilirubin > 3x ULN and any AST) hepatic impairment.

11 DESCRIPTION

TRUQAP (capivasertib) is a kinase inhibitor. The molecular formula for capivasertib is C21H25ClN6O2 and the molecular weight is 428.92 g/mol. The chemical name of capivasertib is 4-amino-N-[(1S)-1-(4-chlorophenyl)-3-hydroxypropyl]-1-(7H-pyrrolo[2,3-d]pyrimidin-4-yl)-4-piperidinecarboxamide. Capivasertib is a white to off-white powder with pH-dependent solubility. It is freely soluble in water at pH values below 1.2 and practically insoluble at pH values above 6.8. Capivasertib has the following structural formula:

TRUQAP film-coated tablets are supplied for oral administration with 160 mg or 200 mg capivasertib. The tablets also contain croscarmellose sodium, dibasic calcium phosphate, magnesium stearate, and microcrystalline cellulose. The film coat contains the following inactive ingredients: copovidone, hypromellose, iron oxide black, iron oxide red, iron oxide yellow, medium chain triglycerides, polydextrose, polyethylene glycol 3350, and titanium dioxide.

12 CLINICAL PHARMACOLOGY

12.1 Mechanism of Action

Capivasertib is an inhibitor of all 3 isoforms of serine/threonine kinase AKT (AKT1, AKT2 and AKT3) and inhibits phosphorylation of downstream AKT substrates. AKT activation in tumors is a result of activation of upstream signaling pathways, mutations in AKT1, loss of phosphatase and tensin homolog (PTEN) function and mutations in the catalytic subunit alpha of phosphatidylinositol 3-kinase (PIK3CA).

In vitro, capivasertib reduced growth of breast cancer cell lines including those with relevant PIK3CA or AKT1 mutations or PTEN alteration. In vivo, capivasertib alone and in combination with fulvestrant inhibited tumor growth of mouse xenograft models including estrogen receptor positive breast cancer models with alterations in PIK3CA, AKT1, and PTEN.

12.2 Pharmacodynamics

Exposure-Response Relationships

The exposure-response relationship and time course of pharmacodynamic response for the effectiveness of capivasertib have not been fully characterized. Exposure-response relationships were observed for diarrhea (CTCAE Grade 2 to 4), rash (CTCAE Grade 2 to 4) and hyperglycemia (CTCAE Grades 3 or 4) at doses of 80 to 800 mg (0.2 to 2 times the approved recommended dosage).

Cardiac Electrophysiology

At the recommended TRUQAP dose, a mean increase in the QTc interval > 20 ms was not observed.

12.3 Pharmacokinetics

Capivasertib pharmacokinetic parameters are presented as the mean [%coefficient of variation (%CV)], unless otherwise specified. The capivasertib steady-state AUC is 8,069 h·ng/mL (37%) and Cmax is 1,371 ng/mL (30%). Steady-state concentrations are predicted to be attained on the 3rd and 4th dosing day of each week, starting week 2.

Capivasertib plasma concentrations are approximately 0.5% to 15% of the steady state Cmax during the off-dosing days.

Capivasertib AUC and Cmax are proportional with dose over a range of 80 to 800 mg (0.2 to 2 times the approved recommended dosage).

Absorption

Tmax is approximately 1-2 hours. The absolute bioavailability is 29%.

Effect of Food

No clinically meaningful differences in capivasertib pharmacokinetics were observed following administration of TRUQAP with a high-fat meal (approximately 1,000 kcal; fat 60%) or a low-fat meal (approximately 400 kcal; fat 26%).

Distribution

The steady state oral volume of distribution is 1,847 L (36%). Capivasertib plasma protein binding is 78% and the plasma-to-blood ratio is 0.71.

Elimination

The half-life is 8.3 hours, and the steady-state oral clearance is 50 L/h (37% CV). Renal clearance was 21% of total clearance.

Metabolism

Capivasertib is primarily metabolized by CYP3A4 and UGT2B7.

Excretion

Following a single radiolabeled oral dose of 400 mg, the mean total recovery was 45% from urine and 50% from feces.

Specific Populations

No clinically significant differences in capivasertib pharmacokinetics were observed based on race/ethnicity (including White, Asian, Black, American Indian or Alaskan Native, and Native Hawaiian or Other Pacific Islander), sex (88% females), body weight (32 to 150 kg), age (26 to 87 years), mild hepatic impairment (bilirubin ≤ ULN and AST > ULN or bilirubin > 1 to 1.5x ULN), or mild to moderate renal impairment (CLcr 30 to 89 mL/min).

The effect of moderate (bilirubin > 1.5 to 3x ULN and any AST) hepatic impairment is not fully characterized.

TRUQAP has not been studied in patients with severe (bilirubin > 3x ULN and any AST) hepatic impairment or severe renal impairment (CLcr 15 to 29 mL/min).

Drug Interaction Studies

Clinical Studies and Model-Informed Approaches

Effect of Strong and Moderate CYP3A Inhibitors on Capivasertib: Itraconazole (strong CYP3A4 inhibitor) is predicted to increase capivasertib AUC by up to 1.7-fold and Cmax by up to 1.4-fold.

Erythromycin and verapamil (moderate CYP3A inhibitors) are predicted to increase capivasertib AUC by up to 1.5-fold and Cmax by up to 1.3-fold.

Effect of Strong and Moderate CYP3A Inducers on Capivasertib: Rifampicin (strong CYP3A4 inducer) is predicted to decrease capivasertib AUC by 70% and Cmax by 60%.

Efavirenz (moderate CYP3A4 inducer) is predicted to decrease capivasertib AUC by 60% and Cmax by 50%.

Effect of UGT2B7 Inhibitors on Capivasertib: Probenecid (UGT2B7 inhibitor) is not predicted to have a clinically meaningful effect on capivasertib pharmacokinetics.

Effect of Acid Reducing Agents on Capivasertib: Rabeprazole (gastric acid reducing agent) did not have a clinically meaningful effect on capivasertib pharmacokinetics.

Effect of Capivasertib on CYP3A Substrates: Concomitant use of TRUQAP increased midazolam (CYP3A substrate) AUC by 1.8-fold on day 4 and by 1.2-fold on day 7.

Effect of Capivasertib on CYP2D6 Substrates: TRUQAP is predicted to increase desipramine (CYP2D6 substrate) AUC by up to 2.1-fold on day 4.

Effect of Capivasertib on CYP2C9 Substrates: Concomitant use of TRUQAP with warfarin (CYP2C9 substrate) is not predicted to have a clinically meaningful effect on warfarin pharmacokinetics.

Effect of Capivasertib on UGT1A1 Substrates: TRUQAP is predicted to increase raltegravir (UGT1A1 substrate) AUC by up to 1.7-fold on day 4.

In-Vitro Studies

Capivasertib inhibits BCRP, OATP1B1, OATP1B3, OAT3, MATE1, MATE2-K, and OCT2.

13 NONCLINICAL TOXICOLOGY

13.1 Carcinogenesis, Mutagenesis, Impairment of Fertility

In a 2-year rat carcinogenicity study, rats received oral doses up to 30 mg/kg/day in males and 75 mg/kg/day in females (approximately 0.2 times and 0.4 times the human exposure at the recommended dose based on AUC, respectively). While there were no statistically significant increases in tumors, there was an increase in malignant mesothelioma in the testis of male rats at 30 mg/kg/day, which is considered a rare tumor in the tested rat strain.

Capivasertib was genotoxic in the in vivo rat bone marrow micronucleus assay through an aneugenic mechanism. Capivasertib was not mutagenic in vitro in a bacterial reverse mutation (Ames) assay or mouse lymphoma gene mutation assay.

In repeat-dose toxicity studies up to 26 weeks duration in rats and 39 weeks duration in dogs, tubular degeneration in the testes and cellular debris in the epididymides were observed at oral capivasertib doses of 100 mg/kg/day in rats and 15 mg/kg/day in dogs (approximately 1 time the human exposure at the recommended dose of 400 mg twice daily based on AUC). In a male fertility study, capivasertib had no effect on fertility in male rats at oral doses up to 100 mg/kg/day following 10 weeks of treatment. Effects of capivasertib on female fertility have not been studied in animals.

13.2 Animal Toxicology and/or Pharmacology

Oral administration of capivasertib for up to 2 years resulted in islet of Langerhans hypertrophy/ hyperplasia in the pancreas and lens degeneration in rats at doses ≥ 15 mg/kg/day (≥ 0.1 times the human exposure at the recommended dose based on AUC).

14 CLINICAL STUDIES

The efficacy of TRUQAP with fulvestrant was evaluated in CAPItello-291 (NCT04305496), a randomized, double-blind, placebo-controlled, multicenter trial that enrolled 708 adult patients with locally advanced (inoperable) or metastatic HR-positive, HER2-negative (defined as IHC 0 or 1+, or IHC 2+/ISH-) breast cancer of which 289 patients had tumors with eligible PIK3CA/AKT1/PTEN-alterations. Eligible PIK3CA/AKT1 activating mutations or PTEN loss of function alterations were identified in the majority of FFPE tumor specimens using FoundationOne®CDx next-generation sequencing (n=686). All patients were required to have progression on an aromatase inhibitor (AI) based treatment in the metastatic setting or recurrence on or within 12 months of completing (neo) adjuvant treatment with an AI. Patients could have received up to two prior lines of endocrine therapy and up to 1 line of chemotherapy for locally advanced (inoperable) or metastatic disease. Patients were excluded if they had clinically significant abnormalities of glucose metabolism (defined as patients with diabetes mellitus Type 1, Type 2, requiring insulin treatment, or HbA1c ≥8% (63.9 mmol/mol)).

Patients were randomized (1:1) to receive either 400 mg of TRUQAP (n=355) or placebo (n=353), given orally twice daily for 4 days followed by 3 days off treatment each week of 28-day treatment cycle. Fulvestrant 500 mg intramuscular injection was administered on cycle 1 days 1 and 15, and then at day 1 of each subsequent 28-day cycle. Patients were treated until disease progression, or unacceptable toxicity. Randomization was stratified by presence of liver metastases (yes vs. no), prior treatment with CDK4/6 inhibitors (yes vs. no) and geographical region (region 1: US, Canada, Western Europe, Australia, and Israel vs region 2: Latin America, Eastern Europe and Russia vs Region 3: Asia).

The major efficacy outcomes were investigator-assessed progression-free survival (PFS) in the overall population, and in the population of patients whose tumors have PIK3CA/AKT1/PTEN-alterations evaluated according to Response Evaluation Criteria in Solid Tumors (RECIST), version 1.1. Additional efficacy outcome measures were overall survival (OS), investigator assessed objective response rate (ORR) and duration of response (DoR).

A statistically significant difference in PFS was observed in the overall population and the population of patients whose tumors have PIK3CA/AKT1/PTEN-alteration. An exploratory analysis of PFS in the 313 (44%) patients whose tumors did not have a PIK3CA/AKT1/PTEN-alteration showed a HR of 0.79 (95% CI: 0.61, 1.02), indicating that the difference in the overall population was primarily attributed to the results seen in the population of patients whose tumors have PIK3CA/AKT1/PTEN-alteration.

Of the 289 patients whose tumors were PIK3CA/AKT1/PTEN-altered, the median age was 59 years (range 34 to 90); female (99%); White (52%), Asian (29%), Black (1%), American Indian/Alaska Native (0.7%), other races (17%) and 9% were Hispanic/Latino. Eastern Cooperative Oncology Group (ECOG) performance status was 0 (66%) or 1 (34%), and 18% were premenopausal or perimenopausal. Seventy-six percent of patients had an alteration in PIK3CA, 13% had an alteration in AKT1, and 17% had an alteration in PTEN. All patients received prior endocrine-based therapy (100% AI based treatment and 44% received tamoxifen). Seventy-one percent of patients were previously treated with a CDK4/6 inhibitor and 18% received prior chemotherapy for locally advanced (inoperable) or metastatic disease.

Efficacy results for PIK3CA/AKT1/PTEN-altered subgroup are presented in Table 7 and Figure 1. Results from the blinded independent review committee (BICR) assessment were consistent with the investigator assessed PFS results. Overall survival results were immature at the time of the PFS analysis (30% of the patients died).

Table 7: Efficacy Results for CAPItello-291 (Patients with PIK3CA/AKT1/PTEN-Altered Tumors)
 | TRUQAP with fulvestrant N=155 | Placebo with fulvestrant N=134
Investigator-Assessed Progression-Free Survival (PFS)
Number of events (%) | 121 (78%) | 115 (86%)
Median, months (95%CI) | 7.3 (5.5, 9.0) | 3.1 (2.0, 3.7)
Hazard ratio (95% CI) [Stratified Cox proportional hazards model stratified by presence of liver metastases (yes vs no), and prior use of CDK4/6 inhibitors (yes vs no).] | 0.50 (0.38, 0.65)
p-value [Stratified log-rank test stratified by presence of liver metastases (yes vs no), and prior use of CDK4/6 inhibitors (yes vs no).] | <0.0001
Investigator-Assessed Confirmed Objective Response Rate (ORR)
Patients with measurable disease | 132 | 124
ORR (95% CI) | 26% (19, 34) | 8% (4, 14)
Complete response rate | 2.3% | 0
Partial response rate | 23% | 8%
Median DoR, months (95%CI) | 10.2 (7.7, NC [NC = not calculable]) | 8.6 (3.8, 9.2)

Figure 1: Kaplan-Meier Plot of Progression-Free Survival in CAPItello-291 (Investigator Assessment, Patients with PIK3CA/AKT1/PTEN-Altered Tumors)

16 HOW SUPPLIED/STORAGE AND HANDLING

How Supplied

Table 8: TRUQAP 160 mg and 200 mg Tablets
Strength | Description | Package Size and Type | NDC Number
TRUQAP 160 mg | Beige film-coated, round, biconvex tablets debossed with ‘CAV’ above ‘160’ on one side and plain on the reverse supplied in HDPE bottle with child-resistant closure. | Bottle of 64 tablets | 0310-9500-01
TRUQAP 200 mg | Beige film-coated, capsule-shaped, biconvex tablets debossed with ‘CAV 200’ on one side and plain on the reverse supplied in HDPE bottle with child-resistant closure. | Bottle of 64 tablets | 0310-9501-01
TRUQAP 160 mg | Beige film-coated, round, biconvex tablets debossed with ‘CAV’ above ‘160’ on one side and plain on the reverse supplied in a blister with a child‑resistant closure. | Each carton has 4 blister packs (64 tablets total)-each blister pack contains 16 tablets. | 0310-9500-02
TRUQAP 200 mg | Beige film-coated, capsule-shaped, biconvex tablets debossed with ‘CAV 200’ on one side and plain on the reverse supplied in a blister with a child‑resistant closure. | Each carton has 4 blister packs (64 tablets total)-each blister pack contains 16 tablets. | 0310-9501-02

Storage and Handling

Store TRUQAP in original packaging to maintain stability at 20°C to 25°C (68°F to 77°F). Excursions permitted to 15°C to 30°C (59°F to 86°F) [see USP Controlled Room Temperature].

Dispense bottled TRUQAP tablets either in:

- The original bottle.
- A USP equivalent tight container. Instruct patients to keep the unused tablets in the container at 20°C to 25°C (68°F to 77°F) and discard after 45 days.

17 PATIENT COUNSELING INFORMATION

Advise the patient to read the FDA-approved patient labeling (Patient Information).

Hyperglycemia

Advise patients that TRUQAP can cause hyperglycemia and that they will need to monitor their fasting blood glucose periodically during therapy. Advise patients to contact their healthcare provider immediately for signs and symptoms of hyperglycemia (e.g., excessive thirst, urinating more often, blurred vision, mental confusion, difficulty breathing, or increased appetite with weight loss) or ketoacidosis [see Warnings and Precautions (5.1)].

Diarrhea

Advise patients that TRUQAP can cause diarrhea and to start antidiarrheal treatment, increase oral fluids, and notify their healthcare provider if diarrhea occurs while taking TRUQAP [see Warnings and Precautions (5.2)].

Cutaneous Adverse Reactions

Advise patients that TRUQAP can cause cutaneous adverse reactions and to contact their healthcare provider immediately to report new or worsening rash, erythematous and exfoliative skin reactions [see Warnings and Precautions (5.3)].

Embryo-Fetal Toxicity

- Advise females to inform their healthcare provider of a known or suspected pregnancy [see Warnings and Precautions (5.4) and Use in Specific Populations (8.1)]. Advise pregnant women and females of reproductive potential of the potential risk to a fetus.
- Advise females of reproductive potential to use effective contraception during treatment with TRUQAP and for 1 month after the last dose [see Use in Specific Population (8.3)].
- Advise male patients with female partners of reproductive potential to use effective contraception during treatment with TRUQAP and for 4 months after the last dose [see Use in Specific Populations (8.3)].
- Refer to the Full Prescribing Information of fulvestrant for pregnancy and contraception information.

Lactation

Advise women to not breastfeed during treatment with TRUQAP [see Use in Specific Populations (8.2)]. Refer to the Full Prescribing Information of fulvestrant for lactation information.

Dosing Instructions

Instruct patients to take TRUQAP 2 times each day, at about the same times each day, for four days on and 3 days off, with or without food. Swallow the tablet(s) whole with water. Tablets should not be chewed, crushed, or split prior to swallowing. [see Dosage and Administration (2.3)].

Instruct patients that if the dose is missed, it can be taken within 4 hours after the time it is usually taken. If more than 4 hours has passed, skip the dose. Take the next dose at the usual time.

Instruct patients that if they vomit after taking the dose, an additional dose should not be taken. The next dose of TRUQAP should be taken at the usual time [see Dosage and Administration (2.3)].

Drug Interactions

Advise patients to inform their healthcare providers of all concomitant medications, including prescription medicines, over-the-counter medications, vitamins, and herbal products [see Drug Interactions (7.1)].

Grapefruit may interact with TRUQAP. Patients should not consume grapefruit products while taking TRUQAP.

Distributed by:

AstraZeneca Pharmaceuticals LP

Wilmington, DE 19850

TRUQAP is a registered trademark of the AstraZeneca group of companies.

©AstraZeneca 2025

Patient Package Insert

PATIENT INFORMATION

TRUQAP® (TRUE-cap)

(capivasertib)

tablets

What is TRUQAP?

TRUQAP is a prescription medicine used in combination with the medicine fulvestrant to treat adults who have hormone receptor (HR)-positive, human epidermal growth factor receptor 2 (HER2)-negative breast cancer that is advanced or that has spread to other parts of the body (metastatic), with an abnormal “PIK3CA”, “AKT1”, or “PTEN” gene, and whose disease has progressed on or after endocrine therapy.

Your healthcare provider will test your cancer for an abnormal “PIK3CA”, “AKT1”, or “PTEN” gene to make sure that TRUQAP is right for you.

It is not known if TRUQAP is safe and effective in children.

Do not take TRUQAP if you:

Have had a severe allergic reaction to TRUQAP or are allergic to any of the ingredients of TRUQAP. See the end of this leaflet for a list of the ingredients in TRUQAP.

Before you take TRUQAP, tell your healthcare provider about all of your medical conditions, including if you:

- have a history of high levels of sugar in your blood or diabetes.
- have a history of rash or other skin disorders.
- have liver problems.
- have any current infection.
- are pregnant or plan to become pregnant. TRUQAP can harm your unborn baby.
Females who are able to become pregnant:
  ∘ Your healthcare provider will check to see if you are pregnant before you start treatment with TRUQAP.
  ∘ You should use effective birth control during treatment with TRUQAP and for 1 month after the last dose. Talk to your healthcare provider about birth control methods that may be right for you during this time.
  ∘ If you become pregnant or think you are pregnant, tell your healthcare provider right away.
Males with female partners who are able to become pregnant should use effective birth control during your treatment with TRUQAP and for 4 months after the last dose. If your female partner becomes pregnant, tell your healthcare provider right away.
- are breastfeeding or plan to breastfeed. Do not breastfeed during treatment with TRUQAP. Talk to your healthcare provider about the best way to feed your baby during treatment with TRUQAP.

Tell your healthcare provider about all the medicines you take, including prescription and over-the-counter medicines, vitamins, and herbal supplements. TRUQAP may affect the way other medicines work, and other medicines may affect how TRUQAP works.

Know the medicines you take. Keep a list of them to show your healthcare provider or pharmacist when you get a new medicine.

How should I take TRUQAP?

- Take TRUQAP exactly as your healthcare provider tells you.
- Do not change your dose or stop taking TRUQAP unless your healthcare provider tells you.
- Take TRUQAP 2 times each day (about 12 hours apart) in the morning and evening, at about the same times each day.
- Take TRUQAP for 4 days in a row, followed by 3 days not taking TRUQAP each week.
- Take TRUQAP with or without food.
- Swallow TRUQAP tablets whole with water. Do not chew, crush, or split the tablets.
- Do not take any tablets that are broken, cracked, or that look damaged.
- If you miss a dose of TRUQAP, you may still take it within 4 hours from the time you usually take it. If it has been more than 4 hours after you usually take your dose, skip that dose. Take the next dose at your usual time. Do not take 2 doses at the same time to make up for a missed dose.
- If you vomit after taking a dose of TRUQAP, do not take an additional dose. Take your next dose at your usual time.
- For women who have not reached menopause or are just starting menopause, your healthcare provider will prescribe a medicine called a luteinizing hormone-releasing hormone (LHRH) agonist to take with TRUQAP and fulvestrant. For men, your healthcare provider may prescribe a LHRH agonist to take with TRUQAP and fulvestrant.

What are the possible side effects of TRUQAP?

TRUQAP may cause severe side effects, including:

- High blood sugar levels (hyperglycemia) - Hyperglycemia is common with TRUQAP and may be severe. Untreated severe hyperglycemia can lead to a condition called diabetic ketoacidosis that can happen in people treated with TRUQAP. Diabetic ketoacidosis is a serious condition that requires treatment in a hospital and that can lead to death. Your healthcare provider will monitor your blood sugar levels before you start and during treatment with TRUQAP. It is not known if TRUQAP is safe in people with type 1 diabetes or people who use insulin to treat their diabetes. Your healthcare provider will monitor your blood sugar levels more often if you have a history of diabetes. Tell your healthcare provider right away if you develop symptoms of hyperglycemia,:

∘ excessive thirst
∘ dry mouth
∘ more frequent urination than usual or a bigger amount of urine than normal
∘ blurred vision
∘ increased appetite with weight loss
∘ stomach area (abdominal) pain
∘ unusual tiredness

∘ confusion
∘ nausea
∘ vomiting
∘ fruity odor on breath
∘ dry or flushed skin
∘ difficulty breathing
∘ sleepiness

- Diarrhea. Diarrhea is common during treatment with TRUQAP and may be severe. Severe diarrhea can lead to the loss of too much body water (dehydration). Tell your healthcare provider if you develop any signs of diarrhea, including loose or watery stool. Your healthcare provider will tell you to drink more fluids or take medicines to treat diarrhea.
- Skin reactions. Skin reactions are common with TRUQAP and can be severe. Tell your healthcare provider or get medical help right away if you get a new or worsening rash, reddening of the skin, fever, blistering of the lips, eyes or mouth, blisters on the skin, skin peeling, or dry skin.

Your healthcare provider may tell you to decrease your dose, temporarily stop your treatment, or completely stop your treatment with TRUQAP if you get certain serious side effects.

The most common side effects of TRUQAP include:

  ∘ nausea
  ∘ tiredness
  ∘ vomiting

∘ mouth sores
∘ changes in certain blood tests

These are not all of the possible side effects of TRUQAP. Call your healthcare provider for medical advice about side effects. You may report side effects to the FDA at 1‑800-FDA-1088.

What should I avoid while taking TRUQAP?

- You should not drink grapefruit juice or eat grapefruit during treatment with TRUQAP.

How should I store TRUQAP?

- Store TRUQAP in original packaging at room temperature between 68°F to 77°F (20°C to 25°C).
- Throw away (discard) TRUQAP after 45 days if the tablets are not kept in the original packaging.
- TRUQAP comes in child resistant packaging.

Keep TRUQAP and all medicines out of the reach of children.

General information about the safe and effective use of TRUQAP.

Medicines are sometimes prescribed for purposes other than those listed in a Patient Information leaflet. Do not use TRUQAP for a condition for which it was not prescribed. Do not give TRUQAP to other people, even if they have the same symptoms you have. It may harm them. You can ask your pharmacist or healthcare provider for information about TRUQAP that is written for health professionals.

What are the ingredients in TRUQAP?

Active ingredient: capivasertib.

Inactive ingredients: copovidone, croscarmellose sodium, dibasic calcium phosphate, hypromellose, iron oxide black, iron oxide red, iron oxide yellow, magnesium stearate, medium chain triglycerides, microcrystalline cellulose, polydextrose, polyethylene glycol 3350, and titanium dioxide

Distributed by:

AstraZeneca Pharmaceuticals LP

Wilmington, DE 19850

TRUQAP is a registered trademark of the AstraZeneca group of companies.

©AstraZeneca 2025

For more information, go to https://www.TRUQAP.com or call 1-800-236-9933. If you still have questions, contact your healthcare provider.

This Patient Information has been approved by the U.S. Food and Drug Administration. Issued: 02/2025

PRINCIPAL DISPLAY PANEL – 160mg tablets

Rx Only NDC 03109500-01

TRUQAP™

(capivasertib) tablets

160mg

64 film-coated tablets

AstraZeneca

PRINCIPAL DISPLAY PANEL – 200mg tablet

Rx only NDC 0310-9501-01

TRUQAP™

(capivasertib) tablets

200mg

64 film-coated tablets

AstraZeneca